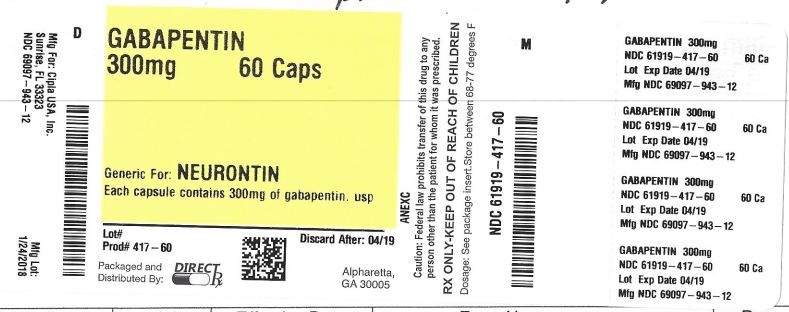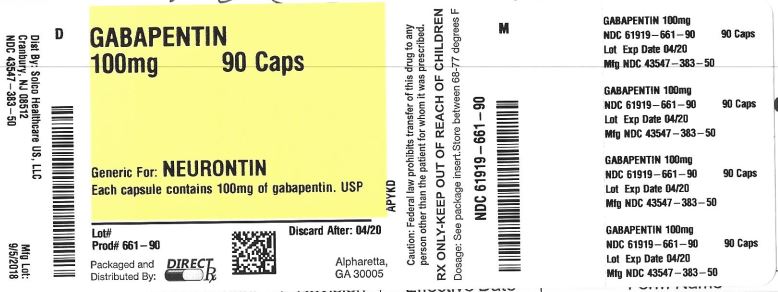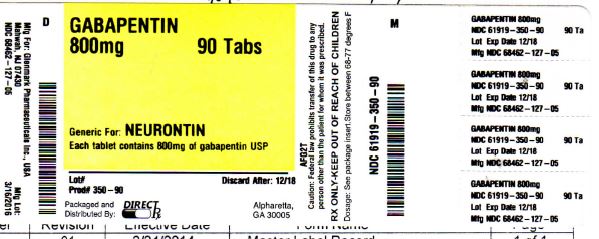 DRUG LABEL: GABAPENTIN
NDC: 61919-350 | Form: TABLET
Manufacturer: DIRECT RX
Category: prescription | Type: HUMAN PRESCRIPTION DRUG LABEL
Date: 20190411

ACTIVE INGREDIENTS: GABAPENTIN 800 mg/1 1
INACTIVE INGREDIENTS: POLYSORBATE 80; STARCH, CORN; COPOVIDONE K25-31; POLOXAMER 407; MAGNESIUM STEARATE; POLYETHYLENE GLYCOL, UNSPECIFIED; HYPROMELLOSES; TALC; TITANIUM DIOXIDE; WATER

GABAPENTIN

MEDICATION GUIDE

Gabapentin Tablets USP

(gab´´ a pen´ tin)

What is the most important information I should know about gabapentin tablets?

Do not stop taking gabapentin tablets without first talking to your healthcare provider.

Stopping gabapentin tablets suddenly can cause serious problems.

Gabapentin tablets can cause serious side effects including:

1. Suicidal Thoughts. Like other antiepileptic drugs, gabapentin tablets may cause suicidal thoughts or actions in a very small number of people, about 1 in 500.
Call a healthcare provider right away if you have any of these symptoms, especially if they are new, worse, or worry you:
•
thoughts about suicide or dying
•
attempts to commit suicide
•
new or worse depression
•
new or worse anxiety
•
feeling agitated or restless
•
panic attacks
•
trouble sleeping (insomnia)
•
new or worse irritability
•
acting aggressive, being angry, or violent
•
acting on dangerous impulses
•
an extreme increase in activity and talking (mania)
•
other unusual changes in behavior or mood
How can I watch for early symptoms of suicidal thoughts and actions?
•
Pay attention to any changes, especially sudden changes, in mood, behaviors, thoughts, or feelings.
•
Keep all follow-up visits with your healthcare provider as scheduled.
Call your healthcare provider between visits as needed, especially if you are worried about symptoms.
Do not stop taking gabapentin tablets without first talking to a healthcare provider.
•
Stopping gabapentin tablets suddenly can cause serious problems. Stopping a seizure medicine suddenly in a patient who has epilepsy can cause seizures that will not stop (status epilepticus).
•
Suicidal thoughts or actions can be caused by things other than medicines. If you have suicidal thoughts or actions, your healthcare provider may check for other causes.
2. Changes in behavior and thinking - Using gabapentin in children 3 to 12 years of age can cause emotional changes, aggressive behavior, problems with concentration, restlessness, changes in school performance, and hyperactivity.
3. Gabapentin tablets may cause serious or life-threatening allergic reactions that may affect your skin or other parts of your body such as your liver or blood cells. This may cause you to be hospitalized or to stop gabapentin. You may or may not have a rash with an allergic reaction caused by gabapentin. Call a healthcare provider right away if you have any of the following symptoms:
•
skin rash
•
hives
•
difficulty breathing
•
fever
•
swollen glands that do not go away
•
swelling of your face, lips, throat, or tongue
•
yellowing of your skin or of the whites of the eyes
•
unusual bruising or bleeding
•
severe fatigue or weakness
•
unexpected muscle pain
•
frequent infections
These symptoms may be the first signs of a serious reaction. A healthcare provider should examine you to decide if you should continue taking gabapentin tablets.

What are gabapentin tablets?

Gabapentin tablets are a prescription medicine used to treat:

•
Pain from damaged nerves (postherpetic pain) that follows healing of shingles (a painful rash that comes after a herpes zoster infection) in adults.
•
Partial seizures when taken together with other medicines in adults and children 3 years of age and older with seizures.

Who should not take gabapentin tablets?

Do not take gabapentin tablets if you are allergic to gabapentin or any of the other ingredients in gabapentin tablets. See the end of this Medication Guide for a complete list of ingredients in gabapentin tablets.

What should I tell my healthcare provider before taking gabapentin tablets?

Before taking gabapentin tablets, tell your healthcare provider if you:

•
have or have had kidney problems or are on hemodialysis
•
have or have had depression, mood problems, or suicidal thoughts or behavior
•
have diabetes
•
are pregnant or plan to become pregnant. It is not known if gabapentin can harm your unborn baby. Tell your healthcare provider right away if you become pregnant while taking gabapentin tablets. You and your healthcare provider will decide if you should take gabapentin tablets while you are pregnant.
o
Pregnancy Registry: If you become pregnant while taking gabapentin tablets, talk to your healthcare provider about registering with the North American Antiepileptic Drug (NAAED) Pregnancy Registry. The purpose of this registry is to collect information about the safety of antiepileptic drugs during pregnancy. You can enroll in this registry by calling 1-888-233-2334.
•
are breast-feeding or plan to breast-feed. Gabapentin can pass into breast milk. You and your healthcare provider should decide how you will feed your baby while you take gabapentin tablets.

Tell your healthcare provider about all the medicines you take, including prescription and over-the-counter medicines, vitamins, and herbal supplements.

Taking gabapentin with certain other medicines can cause side effects or affect how well they work. Do not start or stop other medicines without talking to your healthcare provider.

Know the medicines you take. Keep a list of them and show it to your healthcare provider and pharmacist when you get a new medicine.

How should I take gabapentin tablets?

•
Take gabapentin tablets exactly as prescribed. Your healthcare provider will tell you how much gabapentin to take.
o
Do not change your dose of gabapentin tablets without talking to your healthcare provider.
o
If you take gabapentin tablets and break a tablet in half, the unused half of the tablet should be taken at your next scheduled dose. Half tablets not used within 28 days of breaking should be thrown away.
•
Gabapentin tablets can be taken with or without food. If you take an antacid containing aluminum and magnesium, such as Maalox ®, Mylanta ®, Gelusil ®, Gaviscon ®, or Di-Gel ®, you should wait at least 2 hours before taking your next dose of gabapentin tablets.

If you take too much gabapentin, call your healthcare provider or your local Poison Control Center right away at 1-800-222-1222.

What should I avoid while taking gabapentin tablets?

•
Do not drink alcohol or take other medicines that make you sleepy or dizzy while taking gabapentin tablets without first talking with your healthcare provider. Taking gabapentin tablets with alcohol or drugs that cause sleepiness or dizziness may make your sleepiness or dizziness worse.
•
Do not drive, operate heavy machinery, or do other dangerous activities until you know how gabapentin affects you. Gabapentin tablets can slow your thinking and motor skills.

What are the possible side effects of gabapentin tablets?

Gabapentin tablets may cause serious side effects including:

See "What is the most important information I should know about gabapentin tablets?"

•
problems driving while using gabapentin tablets. See "What I should avoid while taking gabapentin tablets?"
•
sleepiness and dizziness, which could increase the occurrence of accidental injury, including falls
•
The most common side effects of gabapentin tablets include:
•
lack of coordination
•
viral infection
•
feeling drowsy
•
nausea and vomiting
•
difficulty with speaking
•
tremor
•
swelling, usually of legs and feet
•
feeling tired
•
fever
•
jerky movements
•
difficulty with coordination
•
double vision
•
unusual eye movement

Tell your healthcare provider if you have any side effect that bothers you or that does not go away.

These are not all the possible side effects of gabapentin tablets. For more information, ask your healthcare provider or pharmacist.

Call your doctor for medical advice about side effects. You may report side effects to FDA at 1-800-FDA-1088.

How should I store gabapentin tablets?

•
Store gabapentin tablets at 25°C (77°F); excursions permitted to 15° to 30°C (59° to 86°F) [see USP Controlled Room Temperature].

Keep gabapentin tablets and all medicines out of the reach of children.

General information about the safe and effective use of gabapentin tablets

Medicines are sometimes prescribed for purposes other than those listed in a Medication Guide. Do not use gabapentin tablets for a condition for which it was not prescribed. Do not give gabapentin tablets to other people, even if they have the same symptoms that you have. It may harm them.

This Medication Guide summarizes the most important information about gabapentin tablets. If you would like more information, talk with your healthcare provider. You can ask your healthcare provider or pharmacist for information about gabapentin tablets that was written for healthcare professionals.

For more information call 1(888)721-7115.

What are the ingredients in gabapentin tablets?

Active ingredient: gabapentin USP

Inactive ingredients corn starch, copovidone, poloxamer 407, magnesium stearate, polyethylene glycol, talc, hypromellose, titanium dioxide, macrogol, polysorbate 80 and purified water.

This Medication Guide has been approved by the U.S. Food and Drug Administration.

Trademarks are the property of their respective owners.

Manufactured by:

Glenmark Pharmaceuticals Ltd.
India

Manufactured for:

Glenmark Pharmaceuticals Inc., USA
Mahwah, NJ 07430

Questions? 1 (888)721-7115
www.glenmarkpharma.com/usa

December 2017

Manufactured by:
ScieGen Pharmaceuticals, Inc.
Hauppauge, NY 11788 USA

Manufactured for:
Solco Healthcare U.S, LLC
Cranbury, NJ 08512, USA

Rev: 11/17